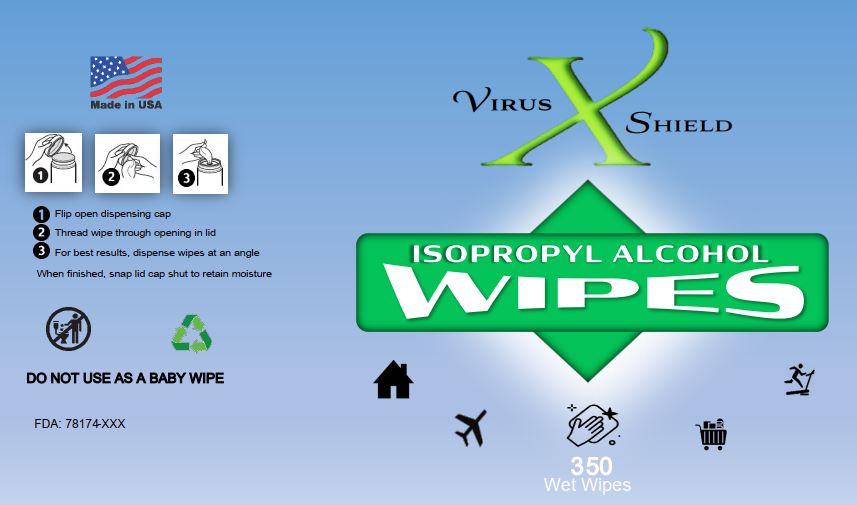 DRUG LABEL: Virus Shield Isopropyl Alcohol Wipes
NDC: 78174-011 | Form: CLOTH
Manufacturer: Custom Chemical Services, LLC
Category: otc | Type: HUMAN OTC DRUG LABEL
Date: 20210102

ACTIVE INGREDIENTS: ISOPROPYL ALCOHOL 80.0852 L/100 L
INACTIVE INGREDIENTS: WATER 19.9148 L/100 L

Active Ingredient:

Isopropyl Alcohol 80% v/v

Purpose

Antibacterial

Use(s)

Hand sanitizer to help reduce bacteria on the skin. Recommended for repeated use.

Warnings

Flammable. Keep away from heat or flame. For external use only.

When using this product avoid contact with eyes, ears, and mouth. In case of contact with eyes, flush eyes with water immediately.
Avoid contact with broken skin. Discontinue use if irritation or redness develops. If condition persists, consult a doctor.

KEEP OUT OF REACH OF CHILDREN.

DO NOT DRINK. NOT EDIBLE. In case of accidental
ingestion, seek professional assistance or contact a
Poison Control Center immediately.

DOSAGE AND ADMINISTRATION

Directions for use: Remove excess dirt. Wet
surface and allow to dry.

It is a violation of Federal Law to use this product

in a manner inconsistent with its labeling.

Inactive Ingredients: Purified water

PACKAGE LABEL

PACKAGED & DISTRIBUTED BY

Custom Chemical Services, LLC

8230 FM 2004

Hitchcock, TX 77563

(409) 925-7818